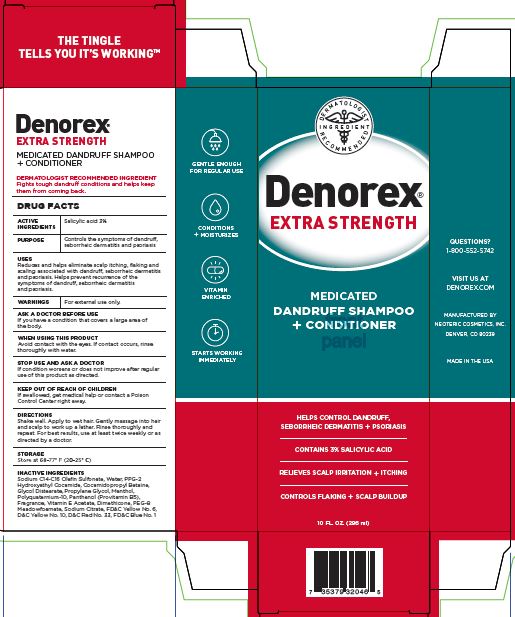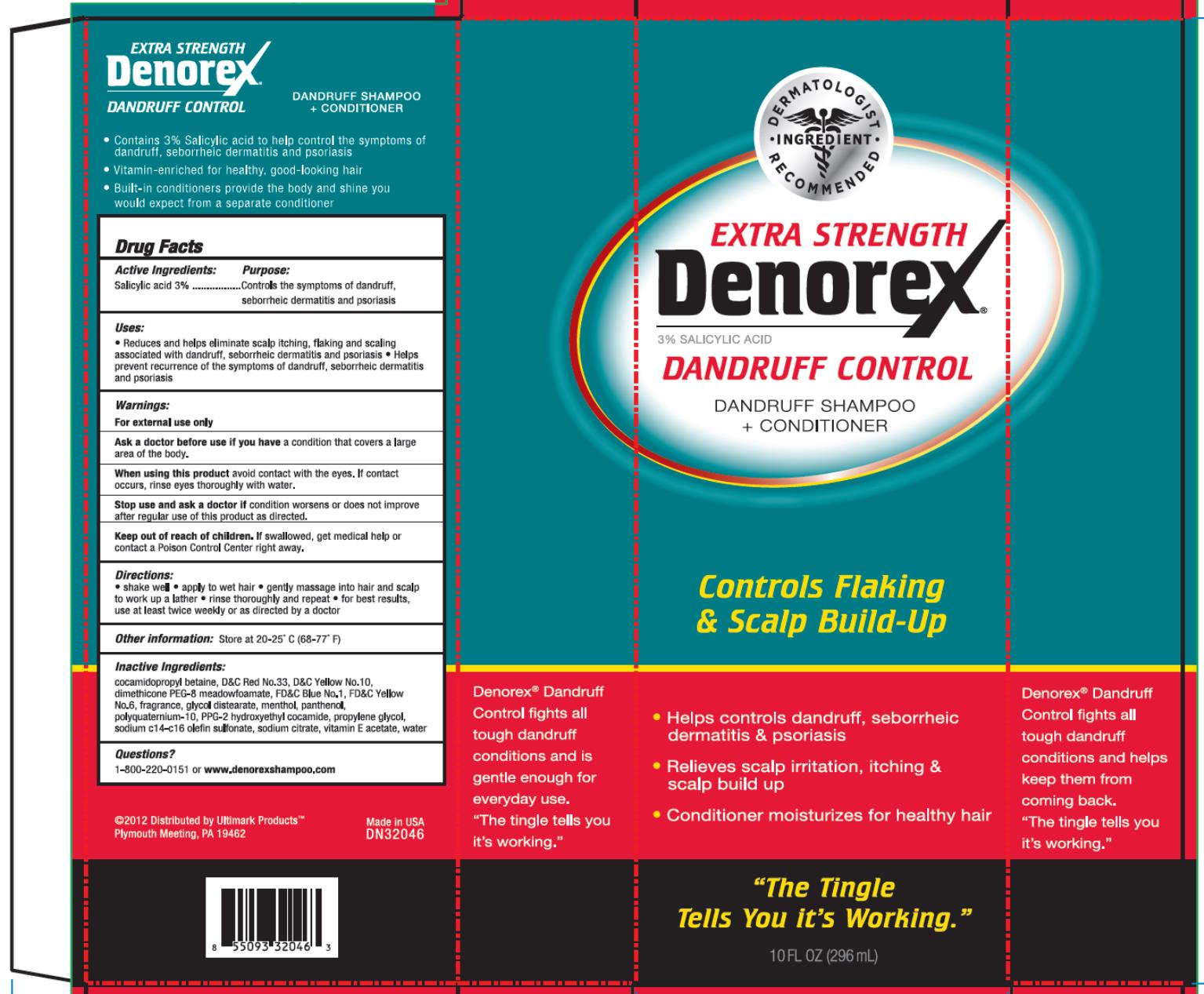 DRUG LABEL: Denorex Extra Strength
NDC: 0395-0059 | Form: SHAMPOO
Manufacturer: Humco Holding Group, Inc.
Category: otc | Type: HUMAN OTC DRUG LABEL
Date: 20200619

ACTIVE INGREDIENTS: SALICYLIC ACID 0.03 g/1 mL
INACTIVE INGREDIENTS: WATER; SODIUM C14-16 OLEFIN SULFONATE; PROPYLENE GLYCOL; GLYCOL DISTEARATE; MENTHOL; COCAMIDOPROPYL BETAINE; PANTHENOL; .ALPHA.-TOCOPHEROL ACETATE; SODIUM CITRATE; FD&C YELLOW NO. 6; D&C YELLOW NO. 10; D&C RED NO. 33; FD&C BLUE NO. 1

Denorex Extra Strength

Drug Facts

Active Ingredients:

Salicylic acid 3%

Purpose

Controls the symptoms of dandruff, seborrheic dermatitis and psoriasis

Uses

- Reduces and helps eliminate scalp itching, flaking and scaling associated with dandruff, seborrheic dermatitis and psoriasis
- Helps prevent recurrence of the symptoms of dandruff, seborrheic dermatitis and psoriasis

Warnings

For external use only.

Ask a doctor before use if you have

a condition that covers a large area of the body.

When using this product

avoid contact with the eyes. If contact occurs, rinse eyes thoroughly with water.

Stop use and ask a doctor if

condition worsens or does not improve after regular use of this product as directed.

Keep out of reach of children.

If swallowed, get medical help or contact a Poison Control Center right away.

Directions

- Shake well
- apply to wet hair
- gently massage into hair and scalp to work up a lather
- rinse thoroughly and repeat
- for best results, use at least twice weekly or as directed by a doctor

Other information

Store at 20º-25º C (68º – 77º F)

Inactive ingredients

cocamidopropyl betaine, D&C Red No. 33, D&C Yellow No. 10, dimethicone PEG-8 meadowfoamate, FD&C Blue No. 1, FD&C Yellow No. 6, fragrance, glycol distearate, menthol, panthenol, polyquaternium-10, PPG-2 hydroxyethyl cocamide, propylene glycol, sodium C14-C16 olefin sulfonate, sodium citrate, vitamin E acetate, water

Questions?

1-800-220-0151

www.denorex.net